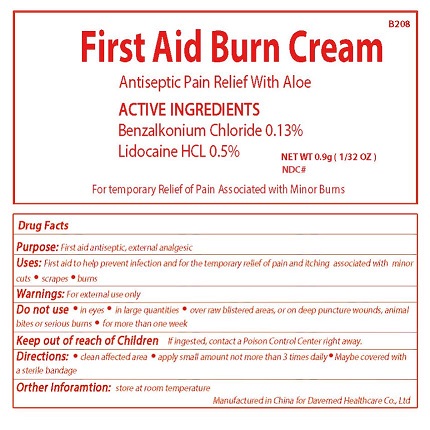 DRUG LABEL: First Aid Burn Cream
NDC: 70897-001 | Form: CREAM
Manufacturer: Davemed Healthcare Co., Ltd
Category: otc | Type: HUMAN OTC DRUG LABEL
Date: 20200203

ACTIVE INGREDIENTS: LIDOCAINE HYDROCHLORIDE 0.5 g/100 g; BENZALKONIUM CHLORIDE 0.13 g/100 g
INACTIVE INGREDIENTS: BENZYL ALCOHOL; DISODIUM EDTA-COPPER; GLYCERYL STEARATE SE; MINERAL OIL; METHYL PARAOXON; PETROLATUM; DIISOPROPYL PARAOXON; ALLANTOIN; TRIETHANOLAMINE SULFATE; STEARIC ACID D7; WATER; SODIUM LAURYL SULFATE; STEARYL ALCOHOL

First Aid Burn Cream

Active Ingredients

Active Ingredient

Lidocaine HCL 0.5%

Benzalkonium Chloride 0.13%

Purpose

First aid antiseptic, external analgesic

Temporary relief of pain associated with minor burns

Uses

First aid to help prevent infection and for the temporary relief of pain and itching associated with minor cuts, scrapes and burns.

WARNINGS

EXTERNAL USE ONLY

KEEP OUT OF REACH OF CHILDREN

If ingested, get medical help or contact a Poison Control Center right away.

DO NOT USE

- in eyes
- in large quantities
- over raw blistered areas or on deep punctured wounds, animal bites or serious burns
- for more than one week

Directions

- Clean affected area
- apply small amount not more than 3 times daily
- maybe covered with a sterile bondage

Inactive ingredients

inactive ingredient

Other Information

Store at room temperature